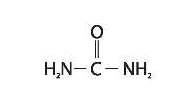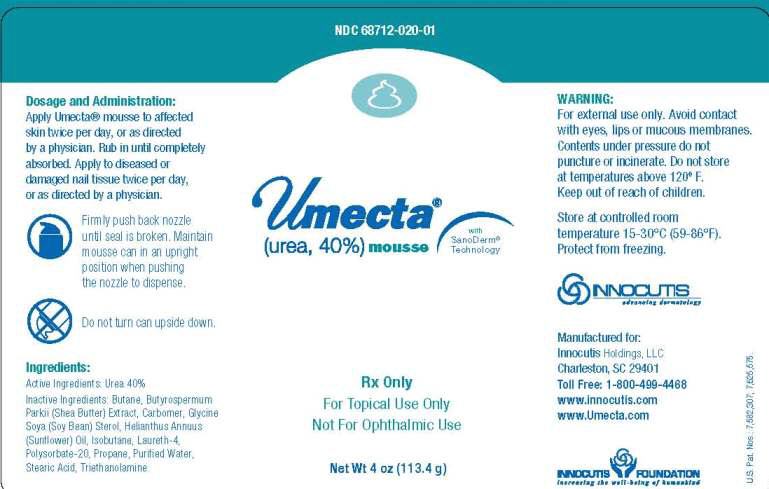 DRUG LABEL: Umecta Mousse
NDC: 71403-020 | Form: AEROSOL, FOAM
Manufacturer: EPI Health, Inc
Category: prescription | Type: HUMAN PRESCRIPTION DRUG LABEL
Date: 20171227

ACTIVE INGREDIENTS: UREA 400 mg/1 g
INACTIVE INGREDIENTS: BUTANE; SHEA BUTTER; CARBOMER HOMOPOLYMER TYPE B (ALLYL SUCROSE CROSSLINKED); SOYBEAN OIL; SUNFLOWER OIL; ISOBUTANE; LAURETH-4; POLYSORBATE 20; PROPANE; WATER; STEARIC ACID; TROLAMINE

Umecta Mousse PI

Description

Rx only
For topical use only
Not for ophthalmic use
Umecta is a keratolytic, emollient which is a gentle, yet potent, tissue softener for nails and skin Each gram of Umecta mousse contains urea (40%), Butane, Butyrospermum Parkii (Shea Butter) Extract, Carbomer, Glycine Soya (Soy Bean) Sterol, Helianthus Annuus (Sunflower) Oil, Isobutane, Laureth-4, Polysorbate-20, Propane, Purified Water, Stearic Acid, Triethanolamine. Urea is a diamide of carbonic acid with the following chemical structure:

Clinical Pharmacology

Urea gently dissolves the intercellular matrix which results in loosening the horny layer of skin and shedding scaly skin at regular intervals, thereby softening hyperkeratotic areas. Urea also hydrates and gently dissolves the intercellular matrix of the nail plate which can result in the softening and eventual debridement of the nail plate.

Pharmacokinetics

The mechanism of action of topically applied urea is not yet known.

Indications and Usage

For debridement and promotion of normal healing of hyperkeratotic surface lesions, particularly where healing is retarded by local infection, necrotic tissue, fibrinous or purulent debris or eschar. Urea is useful for the treatment of hyperkeratotic conditions such as dry, rough skin, dermatitis, psoriasis, xerosis, ichthyosis, eczema, keratosis, keratoderma, corns, and calluses, as well as damaged, ingrown and devitalized nails.

Contraindications

Known hypersensitivity to any of the listed ingredients.

Warnings

For external use only. Avoid contact with eyes, lips or mucous membranes. Umecta Mousse canister - contents under pressure do not puncture or incinerate. Do not store at temperatures above 120º F.

Precautions

This medication is to be used as directed by a physician and should not be used to treat any condition other than that for which it was prescribed. If redness or irritation occurs, discontinue use.

Pregnancy

Animal reproduction studies have not been conducted with Umecta. It is also not known whether Umecta can cause fetal harm when administered to a pregnant woman or can affect reproductive capacity. Umecta should be given to a pregnant woman only if clearly needed.

Nursing Monthers

It is not known whether or not this drug is secreted in human milk. Because many drugs are secreted in human milk, caution should be exercised when Umecta is administered to a nursing woman.

KEEP THIS AND ALL MEDICATIONS OUT OF THE REACH OF CHILDREN.

Adverse Reactions

Transient stinging, burning, itching, or irritation may occur and normally disappear on discontinuing the medication.

Dosage and Administration

Apply Umecta PD bioadhesive emulsion/topical suspension or Umecta mousse to affected skin twice per day, or as directed by a physician. Rub in until completely absorbed

How Supplied

Umecta (urea, 40%) mousse is available in a: 4 oz. can NDC 68712-020-01

Store at controlled room temperature 15-30°C (59-86°F).

Protect from freezing.

Manufactured for:

Innocutis Holdings LLC
Charleston, SC 29401
Toll Free: 1-800-499-4468
www.innocutis.com
www.umecta.com